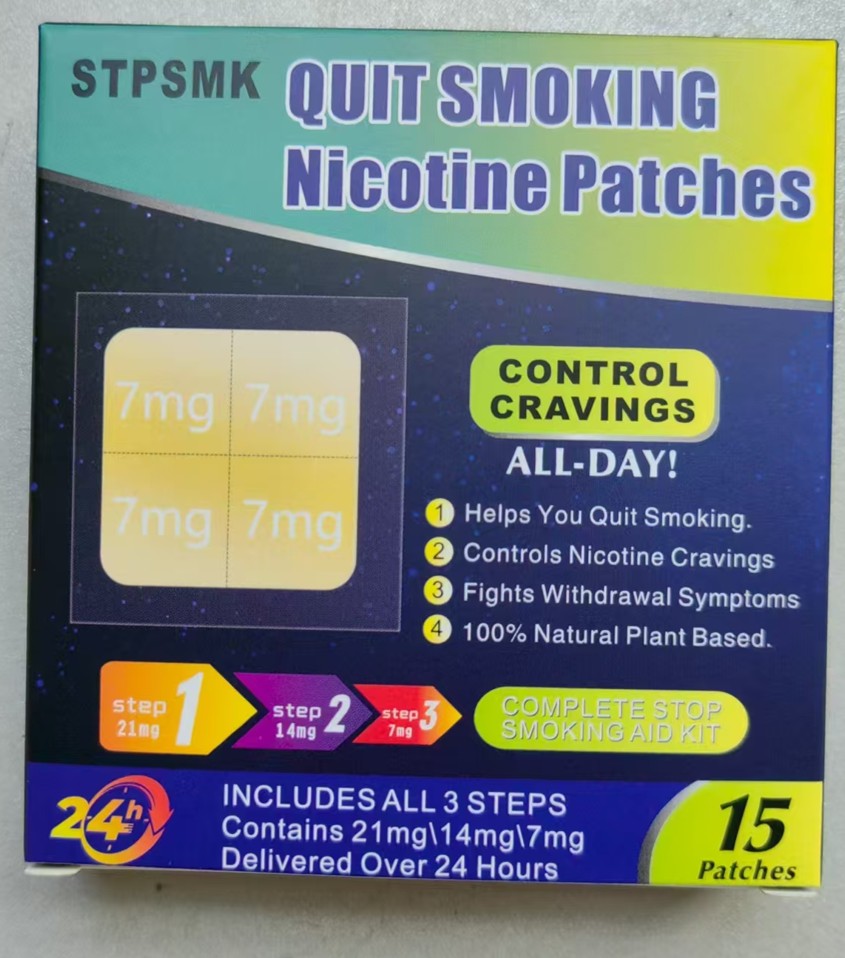 DRUG LABEL: STPSMK QUIT SMOKING NICOTINE PATCHES
NDC: 87231-001 | Form: PATCH
Manufacturer: Guangzhou Ouruisi Biotechnology Co., Ltd
Category: otc | Type: HUMAN OTC DRUG LABEL
Date: 20251116

ACTIVE INGREDIENTS: NICOTINE 28 mg/1 1

87231-001 STPSMK QUIT SMOKING NICOTINE PATCHES

ACTIVE INGREDIENT

nicotine 28mg

PURPOSE

quit smoking

INDICATIONS AND USAGE

Helps You Quit Smoking.
Controls Nicotine Cravings
Fights Withdrawal Symptoms

WARNINGS

For external use only

DO NOT USE

Children and pregnant women are advised not to use it

WHEN USING

Helps You Quit Smoking.

Controls Nicotine Cravings

Fights Withdrawal Symptoms

STOP USE

If you experience discomfort, please stop using and seek medical attention at a hospital.

KEEP OUT OF REACH OF CHILDREN SECTION

DOSAGE AND ADMINISTRATION

step21m9
step14mg
step7m9
COMPLETE STOP
SMOKING AID KIT

INACTIVE INGREDIENT

none